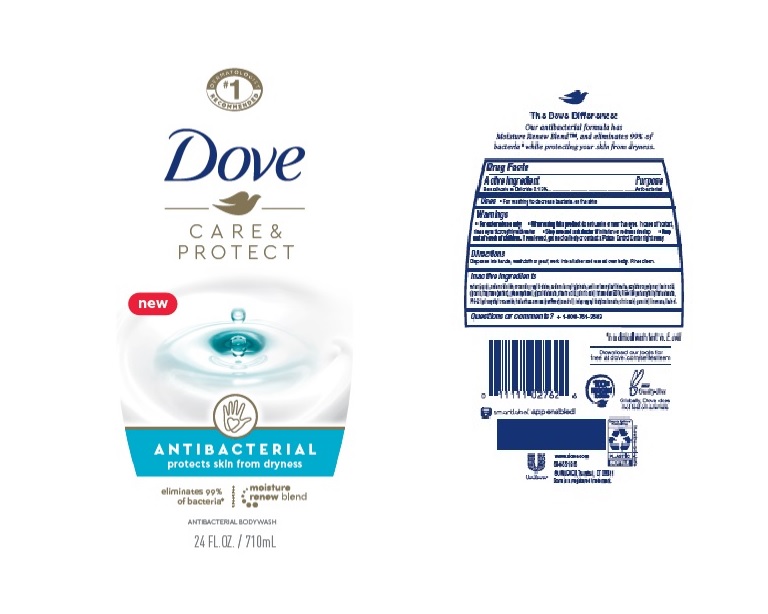 DRUG LABEL: Dove
NDC: 64942-1843 | Form: LIQUID
Manufacturer: Conopco Inc. d/b/a/ Unilever
Category: otc | Type: HUMAN OTC DRUG LABEL
Date: 20241107

ACTIVE INGREDIENTS: BENZALKONIUM CHLORIDE 1.3 mg/1 mL
INACTIVE INGREDIENTS: SODIUM LAUROYL ISETHIONATE; STEARIC ACID; SODIUM CHLORIDE; CITRIC ACID MONOHYDRATE; WATER; GLYCERIN; LIMONENE, (+)-; PALMITIC ACID; EDETATE SODIUM; SUNFLOWER OIL; SODIUM LAUROYL GLYCINATE; GERANIOL; COCAMIDOPROPYL BETAINE; IODOPROPYNYL BUTYLCARBAMATE; PHENOXYETHANOL; GLYCOL DISTEARATE; LAURIC ACID; PEG-150 PENTAERYTHRITYL TETRASTEARATE; PPG-2 HYDROXYETHYL COCAMIDE; LINALOOL, (+/-)-

Dove Care & Protect Moisture Renew Antibacterial Body Wash

DOVE CARE & PROTECT MOISTURE RENEW ANTIBACTERIAL BODY WASH - Benzalkonium Chloride

Dove Care & Protect Moisture Renew Antibacterial Body Wash

Drug Facts

Active ingredient

Benzalkonium Chloride (0.13%)

Purpose

Antibacterial

Uses

For washing to decrease bacteria on the skin

Warnings

• For external use only
• When using this product do not use in or near the eyes. In case of contact, rinse eyes thoroughly with wate r
• Stop use and ask doctor if irritation or redness develop.

• Keep out of reach of children except under adult supervision.

If swallowed, get medical help or contact a poison control Center right away.

Directions

Dispense into hands, wash cloth or pouf, work into lather and use all over body. Rinse clean.

Inactive ingredients

Water, Sodium Chloride, Cocamidopropyl Betaine, Sodium Lauroyl Glycinate, Sodium Lauroyl Isethionate, Acrylates Copolymer, Lauric Acid, Glycerin, Fragrance (Parfum), Phenoxyethanol, Glycol Distearate, Stearic Acid, Palmitic Acid, Tetrasodium EDTA, PEG-150 Pentaerythrityl Tetrastearate, PPG-2 Hydroxyethyl Cocamide, Helianthus Annuus (Sunflower) Seed Oil, Iodopropynyl Butylcarbamate, Citric Acid, Geraniol, Limonene, Linalool.

Questions?

Call toll-free 1-800-761-3683